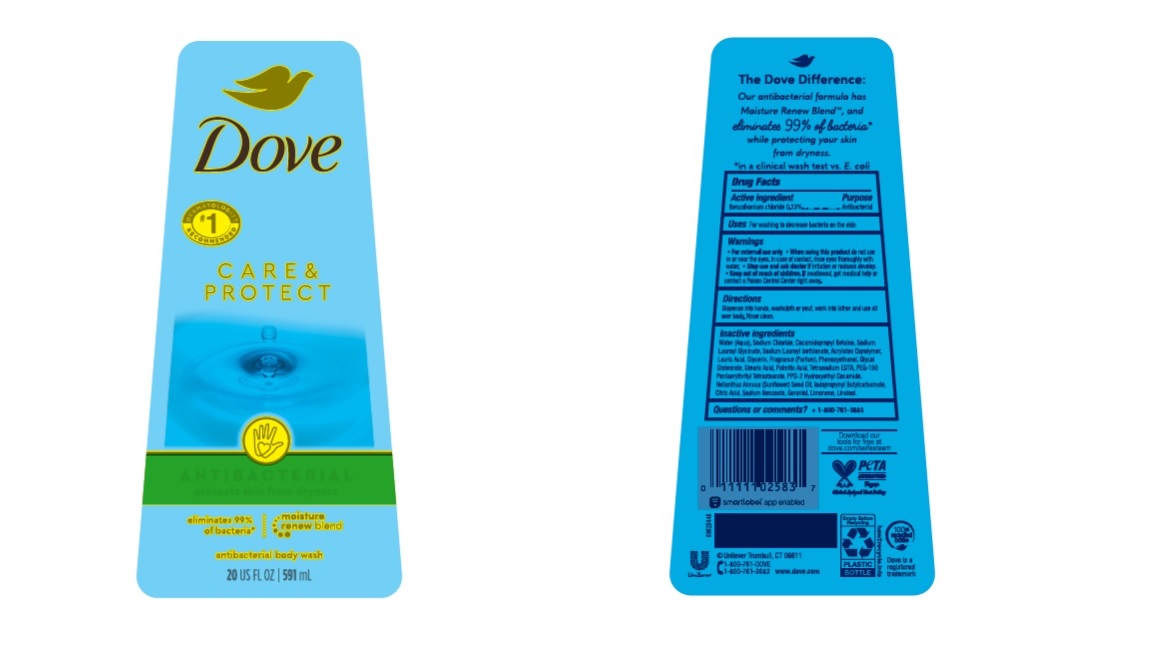 DRUG LABEL: Dove
NDC: 64942-2121 | Form: LIQUID
Manufacturer: Conopco Inc. d/b/a/ Unilever
Category: otc | Type: HUMAN OTC DRUG LABEL
Date: 20241107

ACTIVE INGREDIENTS: BENZALKONIUM CHLORIDE 1.3 mg/1 mL
INACTIVE INGREDIENTS: PHENOXYETHANOL; PPG-2 HYDROXYETHYL COCAMIDE; GERANIOL; LAURIC ACID; PEG-150 PENTAERYTHRITYL TETRASTEARATE; SUNFLOWER OIL; CITRIC ACID MONOHYDRATE; SODIUM LAUROYL ISETHIONATE; SODIUM BENZOATE; PALMITIC ACID; IODOPROPYNYL BUTYLCARBAMATE; STEARIC ACID; SODIUM CHLORIDE; WATER; GLYCERIN; LIMONENE, (+)-; LINALOOL, (+/-)-; COCAMIDOPROPYL BETAINE; GLYCOL DISTEARATE; EDETATE SODIUM

Dove Men+Care Antibactercial Skin Defense Body + Face Wash

Drug Facts

Active ingredient

Benzalkonium Chloride (0.13%)

Purpose

Antibacterial

Uses

For washing to decrease bacteria on the skin

Warnings

• For external use only
• When using this product do not use in or near the eyes. In case of contact, rinse eyes thoroughly with wate r
• Stop use and ask doctor if irritation or redness develop.

• Keep out of reach of children except under adult supervision.

If swallowed, get medical help or contact a poison control Center right away.

Directions

Dispense into hands, wash cloth or pouf, work into lather and use all over body. Rinse clean.

Inactive ingredients

Water, Sodium Chloride, Cocamidopropyl Betaine, Sodium Lauroyl Isethionate, Acrylates Copolymer, Lauric Acid, Glycerin, Fragrance (Parfum), Phenoxyethanol, Glycol Distearate, Stearic Acid, Palmitic Acid, Tetrasodium EDTA, PEG-150 Pentaerythrityl Tetrastearate, PPG-2 Hydroxyethyl Cocamide, Helianthus Annuus (Sunflower) Seed Oil, Iodopropynyl Butylcarbamate, Citric Acid, Sodium Benzoate, Geraniol, Limonene, Linalool.

Questions or comments?

1-800-761-3683